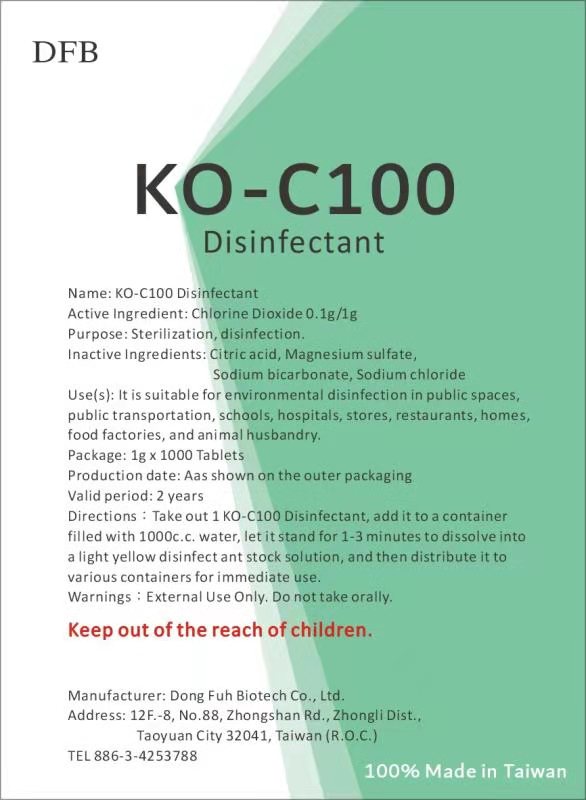 DRUG LABEL: KO-C100
NDC: 81797-701 | Form: TABLET, FOR SOLUTION
Manufacturer: DONG FUH BIOTECH CO., LTD.
Category: otc | Type: HUMAN OTC DRUG LABEL
Date: 20221123

ACTIVE INGREDIENTS: CHLORINE DIOXIDE 0.1 g/1 g
INACTIVE INGREDIENTS: MAGNESIUM SULFATE, UNSPECIFIED; SODIUM BICARBONATE; CITRIC ACID MONOHYDRATE; SODIUM CHLORIDE

DFB, KO-C100

Active Ingredient(s)

Chlorine Dioxide 0.1g/1g. Purpose: Sterilization, disinfection

Purpose

Sterilization, disinfection

Use(s)

It is suitable for environmental disinfection in public spaces, public transportation, schools, hospitals, stores, restaurants, homes, food factories, and animal husbandry.

Warnings

External Use Only. Do not take orally.

Do not use

- in children less than 2 months of age
- on open skin wounds

When using this product keep out of eyes, ears, and mouth. In case of contact with eyes, rinse eyes thoroughly with water.
Stop use and ask a doctor if irritation or rash occurs. These may be signs of a serious condition.
Keep out of reach of children. If swallowed, get medical help or contact a Poison Control Center right away.

Stop use and ask a doctor if irritation or rash occurs. These may be signs of a serious condition.

Keep out of the reach of children.

Directions

Take out 1 KO-100C Disinfectant, add it to a container filled with 1000c.c. water, let it stand for 1-3 minutes to dissolve into a light yellow disinfectant stock solution, and then distribute it to various containers for immediate use.

Other information

- Store at a cool place
- Valid period: 2 years

Inactive ingredients

Citric Acid, Magnesium Sulfate, Sodium Bicarbonate, Sodium Chloride

Package Label - Principal Display Panel

1g * 1000 tablet, NDC: 81797-701-13